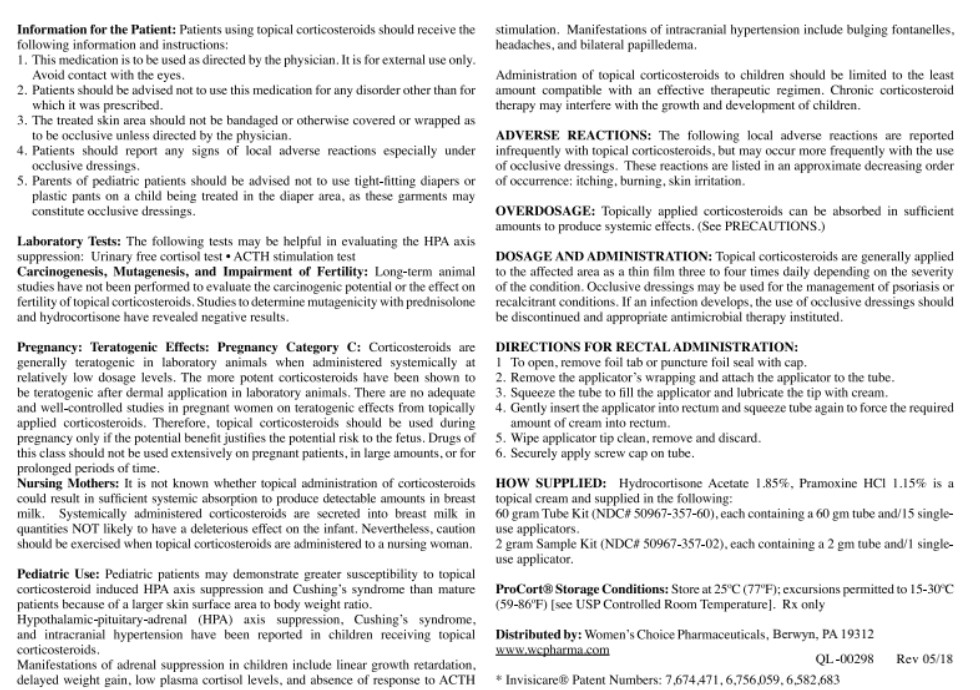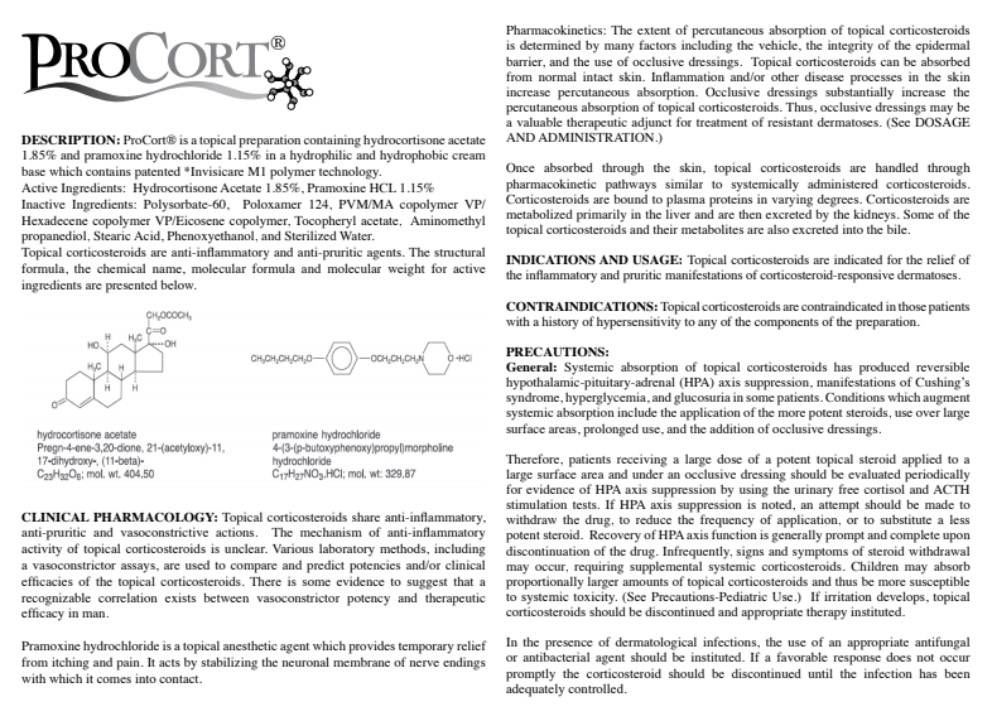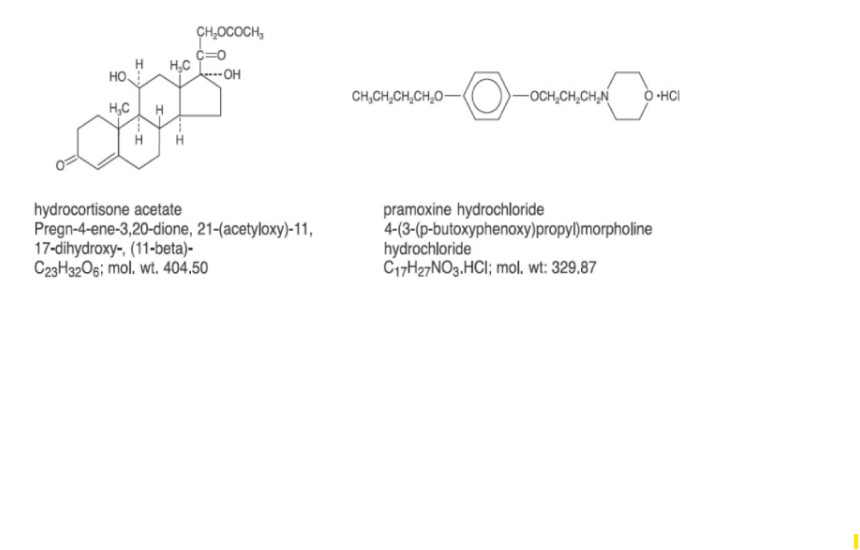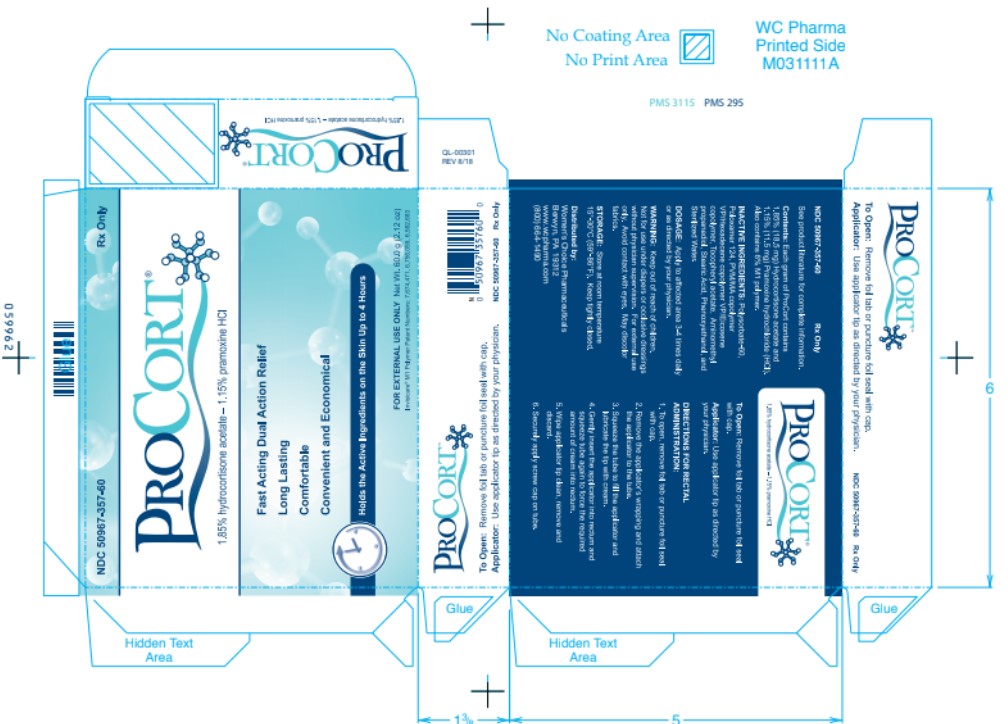 DRUG LABEL: PROCORT
NDC: 50967-357 | Form: CREAM
Manufacturer: Womens Choice Pharmaceuticals LLC
Category: prescription | Type: HUMAN PRESCRIPTION DRUG LABEL
Date: 20250428

ACTIVE INGREDIENTS: HYDROCORTISONE ACETATE 18.5 mg/1 g; PRAMOXINE HYDROCHLORIDE 11.5 mg/1 g
INACTIVE INGREDIENTS: AMINOMETHYL PROPANEDIOL; BUTYL ESTER OF METHYL VINYL ETHER-MALEIC ANHYDRIDE COPOLYMER (125 KD); PHENOXYETHANOL; POLOXAMER 124; POLYSORBATE 60; STEARIC ACID; WATER; ALPHA-TOCOPHEROL

PROCORT (hydrocortisone acetate and pramoxine hydrochloride) cream

PATIENT INFORMATION

PROCORT®

DESCRIPTION:

ProCort® is a topical preparation containing hydrocortisone acetate 1.85% and pramoxine hydrochloride 1.15% in a hydrophilic and hydrophobic cream base which contains patented *Invisicare M1 polymer technology.

Active Ingredients: Hydrocortisone Acetate 1.85%, Pramoxine HCL 1.15%

Inactive Ingredients: Polysorbate-60, Poloxamer 124, PVM/MA copolymer VP/Hexadecene copolymer VP/Eicosene copolymer, Tocopheryl acetate, Aminomethyl propanediol, Stearic Acid, Phenoxyethanol, and Sterilized Water.

Topical corticosteroids are anti-inflammatory and anti-pruritic agents. The structural formula, the chemical name, molecular formula and molecular weight for active ingredients are presented below.

CLINICAL PHARMACOLOGY

Topical corticosteroids share anti-inflammatory,
anti-pruritic and vasoconstrictive actions. The mechanism of anti-inflammatory
activity of topical corticosteroids is unclear. Various laboratory methods, including
a vasoconstrictor assays, are used to compare and predict potencies and/or clinical
efficacies of the topical corticosteroids. There is some evidence to suggest that a
recognizable correlation exists between vasoconstrictor potency and therapeutic
efficacy in man.
Pramoxine hydrochloride is a topical anesthetic agent which provides temporary relief
from itching and pain. It acts by stabilizing the neuronal membrane of nerve endings
with which it comes into contact.

Pharmacokinetics: The extent of percutaneous absorption of topical corticosteroids
is determined by many factors including the vehicle, the integrity of the epidermal
barrier, and the use of occlusive dressings. Topical corticosteroids can be absorbed
from normal intact skin. Inflammation and/or other disease processes in the skin
increase percutaneous absorption. Occlusive dressings substantially increase the
percutaneous absorption of topical corticosteroids. Thus, occlusive dressings may be
a valuable therapeutic adjunct for treatment of resistant dermatoses. (See DOSAGE
AND ADMINISTRATION.)
Once absorbed through the skin, topical corticosteroids are handled through
pharmacokinetic pathways similar to systemically administered corticosteroids.
Corticosteroids are bound to plasma proteins in varying degrees. Corticosteroids are
metabolized primarily in the liver and are then excreted by the kidneys. Some of the
topical corticosteroids and their metabolites are also excreted into the bile.

INDICATIONS AND USAGE

Topical corticosteroids are indicated for the relief of
the inflammatory and pruritic manifestations of corticosteroid-responsive dermatoses.

CONTRAINDICATIONS

Topical corticosteroids are contraindicated in those patients
with a history of hypersensitivity to any of the components of the preparation.

PRECAUTIONS

General: Systemic absorption of topical corticosteroids has produced reversible
hypothalamic-pituitary-adrenal (HPA) axis suppression, manifestations of Cushing’s
syndrome, hyperglycemia, and glucosuria in some patients. Conditions which augment
systemic absorption include the application of the more potent steroids, use over large
surface areas, prolonged use, and the addition of occlusive dressings.
Therefore, patients receiving a large dose of a potent topical steroid applied to a
large surface area and under an occlusive dressing should be evaluated periodically
for evidence of HPA axis suppression by using the urinary free cortisol and ACTH
stimulation tests. If HPA axis suppression is noted, an attempt should be made to
withdraw the drug, to reduce the frequency of application, or to substitute a less
potent steroid. Recovery of HPA axis function is generally prompt and complete upon
discontinuation of the drug. Infrequently, signs and symptoms of steroid withdrawal
may occur, requiring supplemental systemic corticosteroids. Children may absorb
proportionally larger amounts of topical corticosteroids and thus be more susceptible
to systemic toxicity. (See Precautions-Pediatric Use.) If irritation develops, topical
corticosteroids should be discontinued and appropriate therapy instituted.
In the presence of dermatological infections, the use of an appropriate antifungal
or antibacterial agent should be instituted. If a favorable response does not occur
promptly the corticosteroid should be discontinued until the infection has been
adequately controlled.

Information for the Patient: Patients using topical corticosteroids should receive the following information and instructions:

1. This medications is to be used as directed by the physician. It is for external use only. Avoid contact with the eyes.

2. Patients should be advised not to use this medication for any disorder other than for which it was prescribed.

3. The treated skin area should not be bandaged or otherwise covered or wrapped as to be occlusive unless directed by the physician.

4. Patient should report any signs of local adverse reactions especially under occlusive dressings.

5. Parents of pediatric patients should be advised not to use tight-fitting diapers or plastic pants on a child being treated in the diaper area, as these garment may constitute occlusive dressings.

Laboratory Tests: The following tests may be helpful in evaluating the HPA axis suppression: Urinary free cortisol test. ACTH stimulation test

Carcinogenesis, mutagenesis, and Impairment of Fertility: Long-term animal studies have not been performed to evaluate the carcinogenic potential or the effect on fertility of topical corticosteroids. Studies to determine mutagenecity with prednisolone and hydrocortisone have revealed negative results.

Pregnancy: Teratogenic Effects: Pregnancy Category C: Corticosteroids are generally teratogenic in laboratory animals when administered systemically at relatively low dosage levels. The more potent coricosteroids have been shown to be teratogenic after dermal application in laboratory animals. There are no adequate and well-controlled studeis in pregnant women on teratogenic effects from topically applied corticosteroids. Therefore, topical corticosteroids should be used during pregnancy only if the potential benefit justifies the potential risk to the fetus. Drugs of this class should not be used extensively on pregnant patients, in large amounts, or for prolonged periods of time.

Nursing Mothers:It is not known whether topical administration of corticosteroids could result in sufficient systemic absorption to produce detectable amounts in breast milk. Systemically administered corticosteroids are secreted into breast milk in quantitites NOT likely to have deleterious effect on the infant. Nevertheless, caution should be exercised when topical corticosteroids are administered to a nursing woman.

Pediatric Use: Pediatric patients may demonstrate greater susceptibility to topical corticosteroid induced HPA axis suppression and Cushing's syndrome, and intracranial hypertension have been reported in children receiving topical corticosteroids.

Manifestations of adrenal suppression in children include linear growth retardation, delayed weight gain, low plasma cortisol levels, and absence of response to ACTH stimulation. Manifestations of intracranial hypertension include bulging fontanelles, headaches, and bilateral papilledema.

Administration of topical corticosteroids to children should be limited to the least amount compatible with an effective therapeutic regimen. Chronic corticosteroid therapy may interfere with the growth and development of children.

ADVERSE REACTIONS

The following local adverse reactions are reported in frequently with topical corticosteroids, but may occur more frequently with the use of occlusive dressings. These reactions are listed in an approximate decreasing order of occurrence; itching, burning, skin irritation.

OVERDOSAGE

topically applied corticosteroids can be absorbed in sufficient amounts to produce systemic effects. (See precautions.)

DOSAGE AND ADMINISTRATION

topical corticosteroids are generally applied to the affected area as a thin film 3 to 4 times daily, depending on the severity of the condition. Occlusive dressing may be used for the management of psoriasis or recalcitrant conditions. If an infection develops, the use of occlusive dressings should be discontinued and appropriate antimicrobial therapy instituted.
Directions for rectal administration:
1. To open, remove foil, tab or puncture foil seal with cap.
2. Remove the applicator’s wrapping and attach the applicator to the tube.
3. Squeeze the tube to fill the applicator and lubricate the tip with cream.
4. Gently insert the applicator into rectum and squeeze tube begin to force the required amount of cream into rectum.
5. Wipe applicator tip clean remove and discard.
6. Securely apply screw cap on tube.

HOW SUPPLIED

hydrocortisone acetate 1.85%, Pramoxine HCL 1.15% is a topical cream and supplied in the following:
60 gram tube kit (NDC# 50967–357–60), each containing a 60 g tube and/15 single use app applicators.
2 gram Sample Kit (NDC# 50967–357–02), each containing a 2g tube and/1 single use applicator

STORAGE AND HANDLING

ProCort® insert registered symbol,storage condition: store at 25°C (77°F); excursions permitted to 15–30°C (59 to 86°F.)[see USP controlled room temperature]. Rx only.
Distributed by: Women’s Choice, Pharmaceuticals, Berwyn, PA 19312
Www.wcpharma.com

PACKAGE LABEL

ProCort carton for 60g NDC 50967-357-60 Rx Only

See product literature for complete information.

Contents: Each gram of ProCort contains 1.85% (18.5 mg) Hydrocortisone acetate and 1.15% (11.5 mg) Pramoxine hydrochloride (HCI). Also contains 6% M1 polymer. Inactive ingredients: Polysorbate-60, Poloxamer 124, PVM/MA copolymer VP/Hexadecene copolymer VP/Eicosene copolymer, Tocopheryl acetate, Aminomethyl propanediol, Stearic Acid, Phenoxyenthanol, and Sterilized Water.

Dosage: Apply to affected are 3 - 4 times daily or as directed by your physician

Warning: Keep out of reach of children. Not fur use under diapers or occlusive dressings without physician supervision. for externam use only. Avoid contact with eyes. May discolor fabrics.

Storage: Store at room temperature 15°-30°C (59°-86°F). Keep tightly closed.

To Open: Remove foil tab or puncture foil seal with cap.

Applicator: Use applicator tip as directed by your physician.

DIRECTIONS FOR RECTAL ADMINISTRATION:

1. To open, remove foil tab or puncture foil seal with cap.

2. Remove the applicator's wrapping and attach the applicator to the tube.

3. Squeeze the tube to fill the applicator and libricate the tip with cream.

4. Gently insert the applicator into rectum and squeeze tube again to force the required amount of cream into rectum.

5. Wipe applicator tip clean, remove and discard.

6. Securely apply screw cap on tube.

NDC 50967-357-60

ProCort 1.85% hydrocortisone acetate - 1.15% pramoxine HCI

FOR EXTERNAL USE ONLY

Net Weight 60.0g (2.12 oz)

Distributed by: Women's Choice Pharmaceuticals, Gilbert, AZ 85233

www.wcpharma.com

877-774-4949

Invisicare® M1 Plymer Patent Numbers: 7,674,471, 6,756,059, 6,582,683